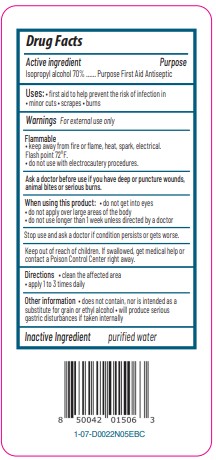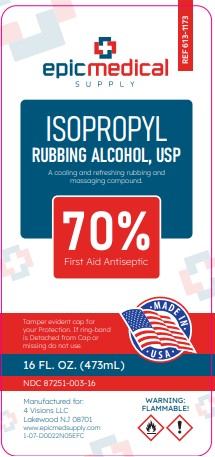 DRUG LABEL: Isopropyl Rubbing Alcohol
NDC: 87251-003 | Form: SOLUTION
Manufacturer: 4 Visions LLC
Category: otc | Type: HUMAN OTC DRUG LABEL
Date: 20260223

ACTIVE INGREDIENTS: ISOPROPYL ALCOHOL 70 mL/100 mL
INACTIVE INGREDIENTS: WATER

Epic Medical Isopropyl Alcohol 70%, USP

Active Ingredient

Isopropyl Alcohol 70%

Purpose

First Aid Antiseptic

Warnings

For external use only

Flammable

Keep away from fire or flame, heat, spark, electrical

Do not use with electrocautery procedures

Ask a doctor before use if you have deep or puncture wounds, animal bites or serious burns

When using this product

do not get into eyes

do ot apply over large areas of the body

do not use longer than 1 week unless directed by a doctor

Stop use and ask a doctor if condition persists or gets worse

Keep out of reach of children.

If swallowed, get medical help or contact a Poison Control Center right away

Directions

Clean the affected area

Apply a small amount of this product 1 to 3 times daily

May be covered with a sterile bandage

If bandaged, let dry first

Other Information

Does not contain, nor is intended as a substitute for grain or ethyl alcohol

Will produce serious gastric disturbances if taken internally

Inactive Ingredient

purified water

PACKAGE LABEL

Epic Medical Supply

Isopropyl Rubbing Alcohol 70%

First Aid Antiseptic

For Rubbing and Massaging

TAMPER EVIDENT CAP FOR YOUR PROTECTION. IF RING-BAND IS DETACHED FROM CAP OR MISSING DO NOT USE.

WARNING FLAMMABLE

Manufactured for:

4 Visions LLC

Lakewood, NJ 08701

www.epicmedicalsupply.com

16 FL OZ (473 mL)